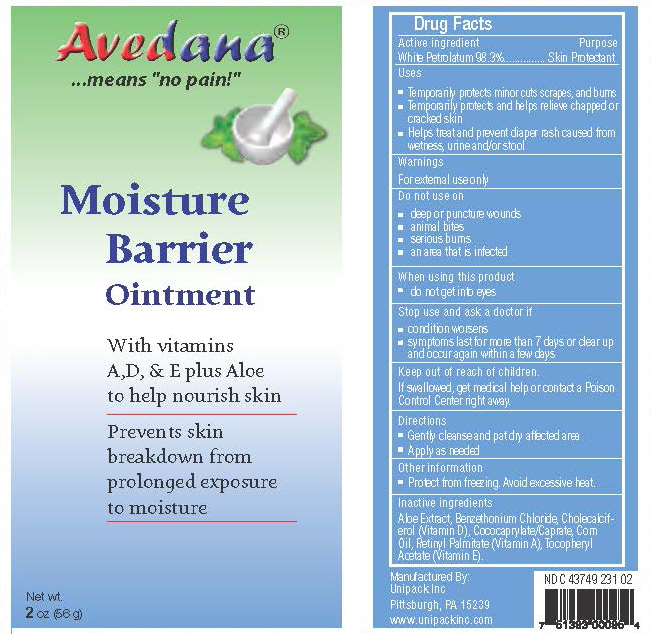 DRUG LABEL: Moisture Barrier
NDC: 43749-231 | Form: OINTMENT
Manufacturer: Unipack LLC
Category: otc | Type: HUMAN OTC DRUG LABEL
Date: 20240213

ACTIVE INGREDIENTS: PETROLATUM 98.3 g/100 g
INACTIVE INGREDIENTS: COCO-CAPRYLATE/CAPRATE; BENZETHONIUM CHLORIDE; ALOE VERA LEAF; ALPHA-TOCOPHEROL ACETATE; CORN OIL; VITAMIN A PALMITATE; CHOLECALCIFEROL

Avedana®Moisture Barrier Ointment (MBO)

Active Ingredient

White Petrolatum 98.3%

Purpose

Skin Protectant

Uses

Temporarily protects minor cuts, scrapes, and burns

Temporarily protects and helps relieve chapped or cracked skin

Helps treat and prevent diaper rash caused from wetness, urine and/or stool

Warnings

For external use only

Do not use on - deep or puncture wounds - animal bites - serious burns - an area that is infected

When using this product - do not get into eyes

Stop use and ask a doctor if - condition worsens - symptoms last for more than 7 days or clear up and occur again within a few days

Keep out of reach of children. If swallowed, get medical help or contact a Poison Control Center right away.

Directions

Gently cleanse and pat dry affected area

Apply as needed

Inactive ingredients

aloe extract, benzethonium chloride, cholecalciferol (vitamin D), cococaprylate / caprate, corn oil, retinyl palmitate (vitamin A), tocopheryl acetate (vitamin E).

Other information

Protect from freezing. Avoid excessive heat.